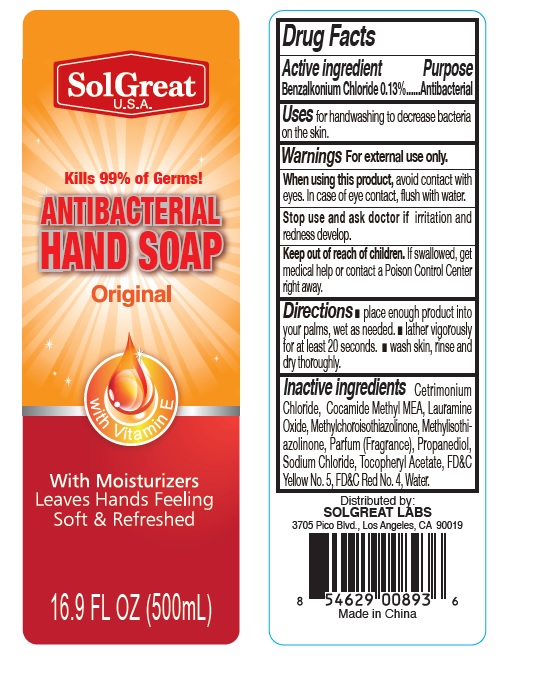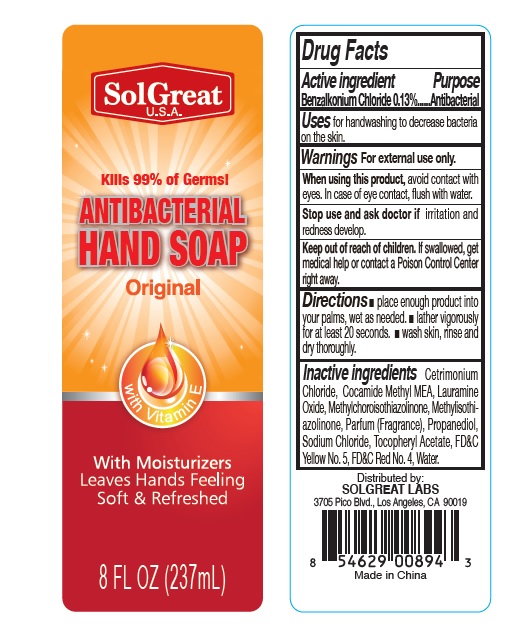 DRUG LABEL: SolGreat Antibacterial handwash
NDC: 73913-003 | Form: LIQUID
Manufacturer: PANATURAL USA, INC.
Category: otc | Type: HUMAN OTC DRUG LABEL
Date: 20200327

ACTIVE INGREDIENTS: BENZALKONIUM CHLORIDE 1.3 mg/1 mL
INACTIVE INGREDIENTS: Cetrimonium chloride; COCOYL METHYL MONOETHANOLAMINE; LAURAMINE OXIDE; METHYLCHLOROISOTHIAZOLINONE; METHYLISOTHIAZOLINONE; PROPANEDIOL; SODIUM CHLORIDE; .ALPHA.-TOCOPHEROL ACETATE; WATER

SolGreat Antibacterial handwash

Active lngredient

Benzalkonium Chloride

Purpose

Antibacterial

Uses

- for handwashing to decrease bacteria on the skin.

Warnings For external use only.

When using this product, avoid contact with eyes. In case of eye contact, flush with water.

Stop use and ask a doctor if irritation and redness develop.

Keep out of reach of children.
If swallowed, get medical help or contact a Poison Control Center right away.

Directions

• place enough product into your palms, wet as needed.
• lather vigorously for at least 20 seconds.
• wash skin, rinse and dry thoroughly.

Inactive ingredients

Cetrimonium Chloride, Cocamide Methyl MEA, Lauramine Oxide, Methylchoroisothiazolinone, Methylisothiazolinone, Parfum (Fragrance), Propanediol, Sodium Chloride, Tocopheryl Acetate, FD&C Yellow No. 5, FD&C Red No. 4, Water.